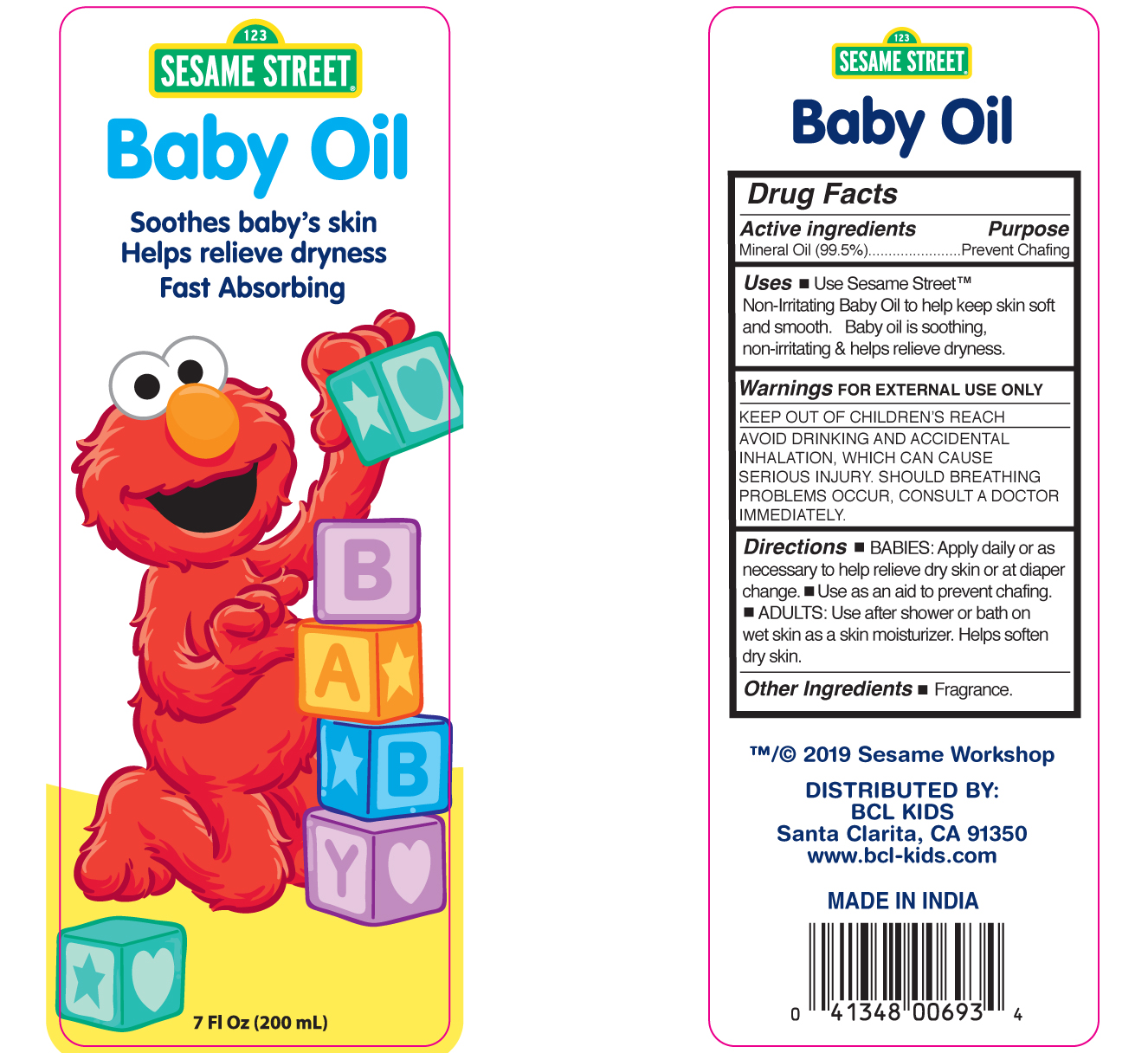 DRUG LABEL: Sesame Street Baby Oil
NDC: 22431-135 | Form: OIL
Manufacturer: Blue Cross Laboratories, Inc.
Category: otc | Type: HUMAN OTC DRUG LABEL
Date: 20190314

ACTIVE INGREDIENTS: MINERAL OIL 99.5 g/100 mL

Sesame street Baby Oil

Active Ingredients Purpose

Mineral Oil (99.5) Prevent chafing

Uses

Use Sesame Street Non-irritatiting Baby Oil to help keep skin soft and smooth. Baby Oil is soothing, non-irritating & helps relieve dryness.

Keep out of children's reach

INDICATIONS AND USAGE

Avoid drinking and accidental inhalationm which can cause Serious injury, Should Breating problems occur, consult a docitor immediately.

Warnings

For external Use only

Directions

Babies: Apply daily or as necessary to help relieve dry skin or at diaper change

use as an aid to prevent chafing

Adults:user after shower or bath on wet skin as a skin moisturizer. Helps soften dry skin

INACTIVE INGREDIENT

Other ingredients

Fragrance

PACKAGE LABEL

Sesame Street Baby Oil

Soothes Baby Skin

Helps relieve dryness

Fast absorbing

7 Fl Oz 200 mL